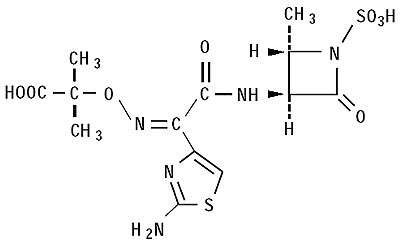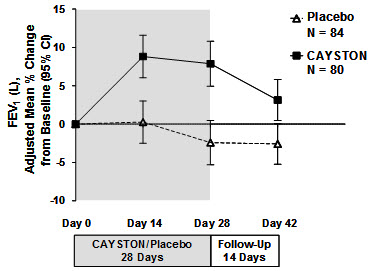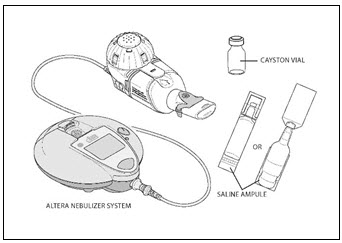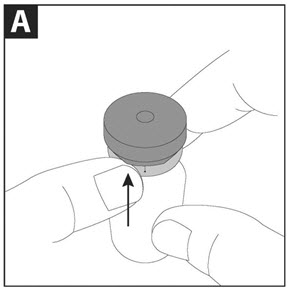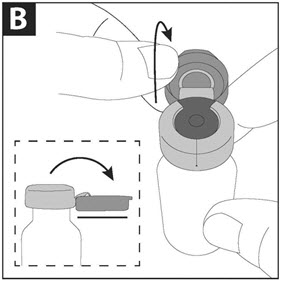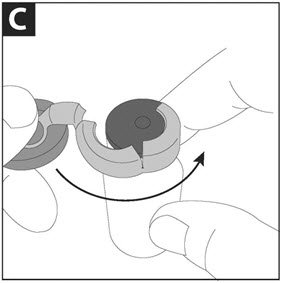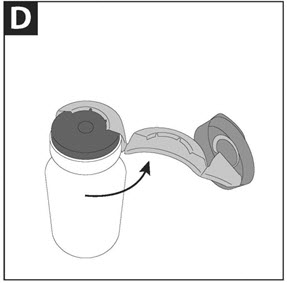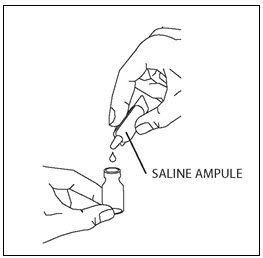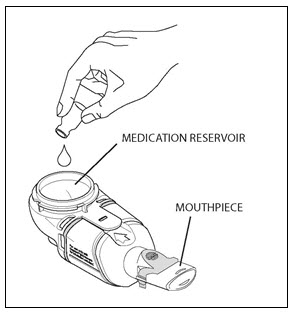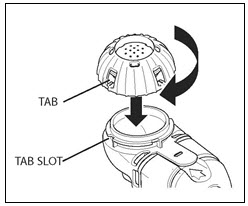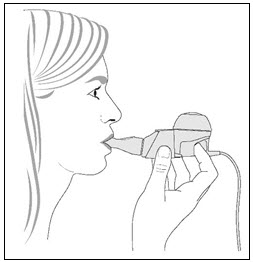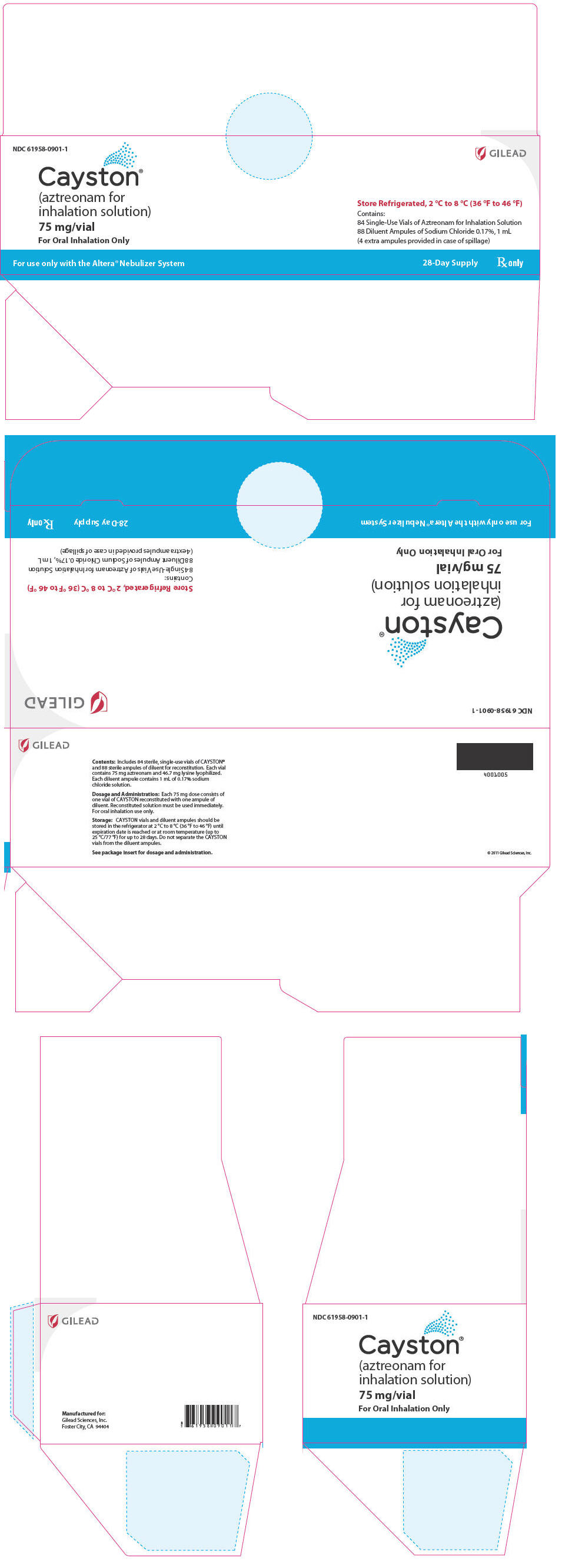 DRUG LABEL: Cayston
NDC: 61958-0901 | Form: KIT | Route: RESPIRATORY (INHALATION)
Manufacturer: Gilead Sciences, Inc.
Category: prescription | Type: HUMAN PRESCRIPTION DRUG LABEL
Date: 20251201

ACTIVE INGREDIENTS: aztreonam 75 mg/1 mL
INACTIVE INGREDIENTS: lysine monohydrate; sodium chloride 1.7 mg/1 mL; water

HIGHLIGHTS OF PRESCRIBING INFORMATION

These highlights do not include all the information needed to use CAYSTON safely and effectively. See full prescribing information for CAYSTON.
CAYSTON® (aztreonam for inhalation solution), for oral inhalation use
Initial U.S. Approval: 1986

MICROBIOLOGY

To reduce the development of drug-resistant bacteria and maintain the effectiveness of CAYSTON and other antibacterial drugs, CAYSTON should be used only to treat patients with cystic fibrosis (CF) known to have Pseudomonas aeruginosa in the lungs.

1 INDICATIONS AND USAGE

CAYSTON is a monobactam antibacterial indicated to improve respiratory symptoms in cystic fibrosis (CF) patients with Pseudomonas aeruginosa. Safety and effectiveness have not been established in pediatric patients below the age of 7 years, patients with FEV1 <25% or >75% predicted, or patients colonized with Burkholderia cepacia. (1)

2 DOSAGE AND ADMINISTRATION

- Administer one dose (one single use vial and one ampule of diluent) 3 times a day for 28 days. (2.1)
- Use dose immediately after reconstitution. (2.2)
- Administer only with the Altera® Nebulizer System. Do not administer with any other type of nebulizer. (2.3)

3 DOSAGE FORMS AND STRENGTHS

- Lyophilized aztreonam (75 mg/vial) (3)
- Diluent (0.17% sodium chloride): 1 mL/ampule (3)

4 CONTRAINDICATIONS

Contraindicated in patients with a known allergy to aztreonam. (4)

5 WARNINGS AND PRECAUTIONS

- Allergic reaction to CAYSTON was seen in clinical trials. Stop treatment if an allergic reaction occurs. Use caution when CAYSTON is administered to patients with a known allergic reaction to beta-lactams. (5.1)
- Bronchospasm has been reported with CAYSTON. Stop treatment if chest tightness develops during nebulizer use. (5.2)

6 ADVERSE REACTIONS

Common adverse reactions (more than 5%) occurring more frequently in CAYSTON patients are cough, nasal congestion, wheezing, pharyngolaryngeal pain, pyrexia, chest discomfort, abdominal pain and vomiting. (6.1)

To report SUSPECTED ADVERSE REACTIONS, contact Gilead Sciences, Inc. at 1-800-GILEAD5, option 3 or FDA at 1-800-FDA-1088 or www.fda.gov/medwatch.

FULL PRESCRIBING INFORMATION

1 INDICATIONS AND USAGE

CAYSTON® is indicated to improve respiratory symptoms in cystic fibrosis (CF) patients with Pseudomonas aeruginosa. Safety and effectiveness have not been established in pediatric patients below the age of 7 years, patients with FEV1 <25% or >75% predicted, or patients colonized with Burkholderia cepacia [see Clinical Studies (14)].

To reduce the development of drug-resistant bacteria and maintain the effectiveness of CAYSTON and other antibacterial drugs, CAYSTON should be used only to treat patients with CF known to have Pseudomonas aeruginosa in the lungs.

2 DOSAGE AND ADMINISTRATION

2.1 Dosing Information

The recommended dose of CAYSTON for both adults and pediatric patients 7 years of age and older is one single-use vial (75 mg of aztreonam) reconstituted with 1 mL of sterile diluent administered 3 times a day for a 28-day course (followed by 28 days off CAYSTON therapy). Dosage is not based on weight or adjusted for age. Doses should be taken at least 4 hours apart.

CAYSTON is administered by inhalation using an Altera® Nebulizer System. Patients should use a bronchodilator before administration of CAYSTON.

2.2 Instructions for CAYSTON Reconstitution

CAYSTON should be administered immediately after reconstitution. Do not reconstitute CAYSTON until ready to administer a dose.

Take one amber glass vial containing CAYSTON and one diluent ampule from the carton. To open the glass vial, carefully remove the blue cap and metal ring and remove the gray rubber stopper. Twist the tip off the diluent ampule and squeeze the liquid into the glass vial. Replace the rubber stopper, then gently swirl the vial until contents have completely dissolved.

The empty vial, stopper, and diluent ampule should be disposed of properly upon completion of dosing.

2.3 Instructions for CAYSTON Administration

CAYSTON is administered by inhalation using an Altera Nebulizer System. CAYSTON should not be administered with any other nebulizer. CAYSTON should not be mixed with any other drugs in the Altera Nebulizer Handset.

CAYSTON is not for intravenous or intramuscular administration.

Patients should use a bronchodilator before administration of CAYSTON. Short-acting bronchodilators can be taken between 15 minutes and 4 hours prior to each dose of CAYSTON. Alternatively, long-acting bronchodilators can be taken between 30 minutes and 12 hours prior to administration of CAYSTON. For patients taking multiple inhaled therapies, the recommended order of administration is as follows: bronchodilator, mucolytics, and lastly, CAYSTON.

To administer CAYSTON, pour the reconstituted solution into the handset of the nebulizer system. Turn the unit on. Place the mouthpiece of the handset in your mouth and breathe normally only through your mouth. Administration typically takes between 2 and 3 minutes. Further patient instructions on how to administer CAYSTON are provided in the FDA-approved patient labeling. Instructions on testing nebulizer functionality and cleaning the handset are provided in the Instructions for Use included with the nebulizer system.

3 DOSAGE FORMS AND STRENGTHS

A dose of CAYSTON consists of a single-use vial of sterile, lyophilized aztreonam (75 mg) reconstituted with a 1 mL ampule of sterile diluent (0.17% sodium chloride). Reconstituted CAYSTON is administered by inhalation.

4 CONTRAINDICATIONS

CAYSTON is contraindicated in patients with a known allergy to aztreonam.

5 WARNINGS AND PRECAUTIONS

5.1 Allergic Reactions

Severe allergic reactions have been reported following administration of aztreonam for injection to patients with no known history of exposure to aztreonam. In addition, allergic reaction with facial rash, facial swelling, and throat tightness was reported with CAYSTON in clinical trials. If an allergic reaction to CAYSTON occurs, stop administration of CAYSTON and initiate treatment as appropriate.

Caution is advised when administering CAYSTON to patients if they have a history of beta-lactam allergy, although patients with a known beta-lactam allergy have received CAYSTON in clinical trials and no severe allergic reactions were reported. A history of allergy to beta-lactam antibiotics, such as penicillins, cephalosporins, and/or carbapenems, may be a risk factor, since cross-reactivity may occur.

5.2 Bronchospasm

Bronchospasm is a complication associated with nebulized therapies, including CAYSTON. Reduction of 15% or more in forced expiratory volume in 1 second (FEV1) immediately following administration of study medication after pretreatment with a bronchodilator was observed in 3% of patients treated with CAYSTON.

5.3 Decreases in FEV1 After 28-Day Treatment Cycle

In clinical trials, patients with increases in FEV1 during a 28-day course of CAYSTON were sometimes treated for pulmonary exacerbations when FEV1 declined after the treatment period. Healthcare providers should consider a patient's baseline FEV1 measured prior to CAYSTON therapy and the presence of other symptoms when evaluating whether post-treatment changes in FEV1 are caused by a pulmonary exacerbation.

5.4 Development of Drug-Resistant Bacteria

Prescribing CAYSTON in the absence of known Pseudomonas aeruginosa infection in patients with CF is unlikely to provide benefit and increases the risk of development of drug-resistant bacteria.

6 ADVERSE REACTIONS

6.1 Clinical Trials Experience

Because clinical trials are conducted under widely varying conditions, adverse reaction rates observed in the clinical trials of drugs cannot be directly compared to rates in the clinical trials of another drug and may not reflect the rates observed in practice.

The safety of CAYSTON was evaluated in 344 patients from two placebo-controlled trials and one open-label follow-on trial. In controlled trials, 146 patients with CF received 75 mg CAYSTON 3 times a day for 28 days.

Table 1 displays adverse reactions reported in more than 5% of patients treated with CAYSTON 3 times a day in placebo-controlled trials. The listed adverse reactions occurred more frequently in CAYSTON-treated patients than in placebo-treated patients.

Table 1 Adverse Reactions Reported in more than 5% of Patients Treated with CAYSTON in the Placebo-Controlled Trials
Event (Preferred Term) | Placebo (N=160) n (%) | CAYSTON 75 mg 3 times a day (N=146) n (%)
Cough | 82 (51%) | 79 (54%)
Nasal congestion | 19 (12%) | 23 (16%)
Wheezing | 16 (10%) | 23 (16%)
Pharyngolaryngeal pain | 17 (11%) | 18 (12%)
Pyrexia | 9 (6%) | 19 (13%)
Chest discomfort | 10 (6%) | 11 (8%)
Abdominal Pain | 8 (5%) | 10 (7%)
Vomiting | 7 (4%) | 9 (6%)

Adverse reactions that occurred in less than 5% of patients treated with CAYSTON were bronchospasm (3%) [see Warnings and Precautions (5.2)] and rash (2%).

6.2 Postmarketing Experience

In addition to adverse reactions reported from clinical trials, the following possible adverse reactions have been identified during post-approval use of CAYSTON. Because these events have been reported voluntarily from a population of unknown size, estimates of frequency cannot be made.

MUSCULOSKELETAL AND CONNECTIVE TISSUE DISORDERS
Arthralgia, joint swelling

7 DRUG INTERACTIONS

No formal clinical studies of drug interactions with CAYSTON have been conducted.

8 USE IN SPECIFIC POPULATIONS

8.1 Pregnancy

Risk Summary

Available data on CAYSTON use in pregnant women is insufficient to inform a drug-associated risk of major birth defects, miscarriage, or adverse maternal or fetal outcomes; however, systemic absorption of aztreonam following inhaled administration is expected to be minimal [see Clinical Pharmacology (12.3)]. There are risks to the mother associated with cystic fibrosis in pregnancy (see Clinical Considerations). In animal reproduction studies with aztreonam for injection administered parenterally to pregnant rats and rabbits during organogenesis, there was no evidence of developmental toxicity. A peri/postnatal study in rats revealed no drug-induced changes in maternal, fetal, or neonatal parameters.

The estimated background risk of major birth defects and miscarriage for the indicated population are unknown. All pregnancies have a background risk of birth defect, loss, or other adverse outcomes. In the U.S. general population, the estimated background risk of major birth defects and miscarriage in clinically recognized pregnancies is 2% to 4% and 15% to 20%, respectively.

Clinical Considerations

Disease-Associated Maternal and/or Embryo/Fetal Risk

Cystic fibrosis may increase the risk for preterm delivery.

Data

Animal Data

No reproductive toxicity studies have been conducted with CAYSTON. However, studies were conducted with aztreonam for injection. No evidence of developmental toxicity has been shown in studies with pregnant rats and rabbits that received parenteral doses of aztreonam during organogenesis of up to 1800 and 1200 mg/kg/day, respectively. In rats receiving aztreonam for injection during late gestation and lactation at up to 1800 mg/kg/day, no drug induced changes in maternal, fetal or neonatal parameters were observed. These animal reproduction and developmental toxicity studies used parenteral routes of administration that would provide systemic exposures significantly greater than the average peak plasma levels measured in humans following CAYSTON therapy.

8.2 Lactation

Risk Summary

Following intravenous administration of aztreonam for injection, aztreonam is excreted in human milk at concentrations that are less than one percent of those determined in simultaneously obtained maternal serum. Peak plasma concentrations of aztreonam following administration of CAYSTON (75 mg) are approximately 1% of peak concentrations observed following IV aztreonam (500 mg). Systemic absorption of aztreonam following inhaled administration is expected to be minimal [see Clinical Pharmacology (12.3)]. There are no data on the effects of aztreonam on the breastfed infant or the effects on milk production. The developmental and health benefits of breastfeeding should be considered along with the mother's clinical need for CAYSTON and any potential adverse effects on the breastfed infant from CAYSTON or from the underlying maternal condition.

8.4 Pediatric Use

Patients 7 years and older were included in clinical trials with CAYSTON. Fifty-five patients under 18 years of age received CAYSTON in placebo-controlled trials. No dose adjustments were made for pediatric patients. Pyrexia was more commonly reported in pediatric patients than in adult patients. Safety and effectiveness in pediatric patients below the age of 7 years have not been established.

8.5 Geriatric Use

Clinical trials of CAYSTON did not include CAYSTON-treated patients aged 65 years of age and older to determine whether they respond differently from younger patients.

8.6 Use in Patients with Renal Impairment

Aztreonam is known to be excreted by the kidney. Placebo-controlled clinical trials with CAYSTON excluded patients with abnormal baseline renal function (defined as serum creatinine greater than 2 times the upper limit of normal range). Given the low systemic exposure of aztreonam following administration of CAYSTON, clinically relevant accumulation of aztreonam is unlikely to occur in patients with renal impairment. Therefore, CAYSTON may be administered to patients with mild, moderate and severe renal impairment with no dosage adjustment.

10 OVERDOSAGE

No overdoses have been reported with CAYSTON in clinical trials to date. In clinical trials, 225 mg doses of CAYSTON via inhalation were associated with higher rates of drug-related respiratory adverse reactions, particularly cough. Since the peak plasma concentration of aztreonam following administration of CAYSTON (75 mg) is approximately 0.6 mcg/mL, compared to a serum concentration of 54 mcg/mL following administration of aztreonam for injection (500 mg), no systemic safety issues associated with CAYSTON overdose are anticipated.

11 DESCRIPTION

A dose of CAYSTON consists of a 2 mL amber glass vial containing lyophilized aztreonam (75 mg) and lysine (46.7 mg), and a low-density polyethylene ampule containing 1 mL sterile diluent (0.17% sodium chloride). The reconstituted solution is for inhalation. The formulation contains no preservatives or arginine.

The active ingredient in CAYSTON is aztreonam, a monobactam antibacterial. The monobactams are structurally different from beta-lactam antibiotics (e.g., penicillins, cephalosporins, carbapenems) due to a monocyclic nucleus. This nucleus contains several side chains; sulfonic acid in the 1-position activates the nucleus, an aminothiazolyl oxime side chain in the 3-position confers specificity for aerobic Gram-negative bacteria including Pseudomonas spp., and a methyl group in the 4-position enhances beta-lactamase stability.

Aztreonam is designated chemically as (Z)-2-[[[(2-amino-4-thiazolyl)[[(2S,3S)-2-methyl-4-oxo-1-sulfo-3-azetidinyl]carbamoyl]methylene]amino]oxy]-2-methylpropionic acid. The structural formula is presented below:

CAYSTON is a white to off-white powder. CAYSTON is sterile, hygroscopic, and light sensitive. Once reconstituted with the supplied diluent, the pH range is 4.5 to 6.0.

12 CLINICAL PHARMACOLOGY

12.1 Mechanism of Action

Aztreonam is an antibacterial drug [see Clinical Pharmacology (12.4)].

12.3 Pharmacokinetics

Sputum Concentrations

Sputum aztreonam concentrations exhibited considerable variability between patients receiving CAYSTON (75 mg) in clinical trials. The mean sputum concentration 10 minutes following the first dose of CAYSTON (n = 195 patients with CF) was 726 mcg/g. Mean sputum concentrations of aztreonam in patients receiving CAYSTON 3 times a day for 28 days were 984 mcg/g, 793 mcg/g, and 715 mcg/g 10 minutes after dose administration on Days 0, 14, and 28, respectively, indicating no accumulation of aztreonam in sputum.

Plasma Concentrations

Plasma aztreonam concentrations exhibited considerable variability between patients receiving CAYSTON (75 mg) in the clinical trials. The mean plasma concentration one hour following the first dose of CAYSTON (at approximately the peak plasma concentration) was 0.59 mcg/mL. Mean peak plasma concentrations in patients receiving CAYSTON 3 times a day for 28 days were 0.55 mcg/mL, 0.67 mcg/mL, and 0.65 mcg/mL on Days 0, 14, and 28, respectively, indicating no systemic accumulation of aztreonam. In contrast, the serum concentration of aztreonam following administration of aztreonam for injection (500 mg) is approximately 54 mcg/mL.

Absorption

Evaluation of plasma and urine aztreonam concentrations following administration of CAYSTON indicates low systemic absorption of aztreonam. Approximately 10% of the total CAYSTON dose is excreted in the urine as unchanged drug, as compared to 60–65% following intravenous administration of aztreonam for injection.

Distribution

The protein binding of aztreonam in plasma is approximately 77% within the clinical dose range of concentrations achieved following CAYSTON administration.

Metabolism

Following intramuscular administration of aztreonam for injection 500 mg every 8 hours for 7 days, approximately 6% of the dose was excreted as a microbiologically inactive open β-lactam ring hydrolysis product in an 8-hour urine collection on the last day of multiple dosing.

Excretion

The elimination half-life of aztreonam from plasma is approximately 2.1 hours following administration of CAYSTON to adult patients with CF, similar to what has been reported for aztreonam for injection. Approximately 10% of the total CAYSTON dose is excreted in the urine as unchanged drug. Systemically absorbed aztreonam is eliminated about equally by active tubular secretion and glomerular filtration. Following administration of a single intravenous dose of radiolabeled aztreonam for injection, about 12% of the dose was recovered in the feces.

12.4 Microbiology

Mechanism of Action

Aztreonam exhibits activity in vitro against Gram-negative aerobic pathogens including P. aeruginosa. Aztreonam binds to penicillin-binding proteins of susceptible bacteria, which leads to inhibition of bacterial cell wall synthesis and death of the cell. Aztreonam activity is not decreased in the presence of CF lung secretions.

Susceptibility Testing

A single sputum sample from a patient with CF may contain multiple morphotypes of P. aeruginosa and each morphotype may have a different level of in vitro susceptibility to aztreonam. There are no in vitro susceptibility test interpretive criteria for isolates of P. aeruginosa obtained from the sputum of CF patients.^1

Development of Resistance

No changes in the susceptibility of P. aeruginosa to aztreonam were observed following a 28-day course of CAYSTON in the placebo-controlled trials.

Cross-Resistance

No cross-resistance to other classes of antibiotics, including aminoglycosides, quinolones, and beta-lactams, was observed following a 28-day course of CAYSTON in the Phase 3 placebo-controlled trials or in an open-label follow-on trial of up to nine 28-day courses of 75 mg CAYSTON 3 times a day.

Other

No trends in the treatment-emergent isolation of other bacterial respiratory pathogens (Burkholderia cepacia, Stenotrophomonas maltophilia, Achromobacter xylosoxidans, and Staphylococcus aureus) were observed in clinical trials. There was a slight increase in the isolation of Candida spp. following up to nine 28-day courses of CAYSTON therapy.

13 NONCLINICAL TOXICOLOGY

13.1 Carcinogenesis, Mutagenesis, Impairment of Fertility

A 104-week rat inhalation toxicology study to assess the carcinogenic potential of aztreonam demonstrated no drug-related increase in the incidence of tumors. Rats were exposed to aerosolized aztreonam for up to 4 hours per day. Peak plasma levels of aztreonam averaging approximately 6.8 mcg/mL were measured in rats at the highest dose level. This is approximately 12-fold higher than the average peak plasma level measured in humans following CAYSTON therapy.

Genetic toxicology studies performed in vitro demonstrated that aztreonam did not induce structural chromosome aberrations in CHO cells and did not induce mutations at the TK locus in mouse lymphoma L5178Y TK+/- cells. In vivo, aztreonam was not clastogenic in mouse bone marrow cells.

Aztreonam did not impair the fertility of rats when administered parenterally at doses up to 2400 mg/kg/day that would provide systemic exposures significantly higher than peak plasma levels measured in humans following CAYSTON therapy.

14 CLINICAL STUDIES

CAYSTON was evaluated over a period of 28 days of treatment in a randomized, double-blind, placebo-controlled, multicenter trial that enrolled patients with CF and P. aeruginosa. This trial was designed to evaluate improvement in respiratory symptoms. Patients 7 years of age and older and with FEV1 of 25% to 75% predicted were enrolled. All patients received CAYSTON or placebo on an outpatient basis administered with the Altera Nebulizer System. All patients were required to take a dose of an inhaled bronchodilator (beta-agonist) prior to taking a dose of CAYSTON or placebo. Patients were receiving standard care for CF, including drugs for obstructive airway diseases.

The trial enrolled 164 patients with CF and P. aeruginosa. The mean age was 30 years, and the mean baseline FEV1 % predicted was 55%; 43% were females and 96% were Caucasian. These patients were randomized in a 1:1 ratio to receive either CAYSTON (75 mg) or volume-matched placebo administered by inhalation 3 times a day for 28 days. Patients were required to have been off antibiotics for at least 28 days before treatment with study drug. The primary efficacy endpoint was improvement in respiratory symptoms on the last day of treatment with CAYSTON or placebo. Respiratory symptoms were also assessed two weeks after the completion of treatment with CAYSTON or placebo. Changes in respiratory symptoms were assessed using a questionnaire that asks patients to report on symptoms like cough, wheezing, and sputum production.

Improvement in respiratory symptoms was noted for CAYSTON-treated patients relative to placebo-treated patients on the last day of drug treatment. Statistically significant improvements were seen in both adult and pediatric patients but were substantially smaller in adult patients. Two weeks after completion of treatment, a difference in respiratory symptoms between treatment groups was still present, though the difference was smaller.

Pulmonary function, as measured by FEV1 (L), increased from baseline in patients treated with CAYSTON (see Figure 1). The treatment difference at Day 28 between CAYSTON-treated and placebo-treated patients for percent change in FEV1 (L) was statistically significant at 10% (95% CI: 6%, 14%). Improvements in FEV1 were comparable between adult and pediatric patients. Two weeks after completion of drug treatment, the difference in FEV1 between CAYSTON and placebo groups had decreased to 6% (95% CI: 2%, 9%).

Figure 1 Adjusted Mean Percent Change in FEV1 from Baseline to Study End (Days 0–42)

15 REFERENCES

1. Clinical and Laboratory Standards Institute (CLSI). Methods for Dilution Antimicrobial Susceptibility Tests for Bacteria that Grow Aerobically—Eighth Edition; Approved Standard. CLSI Document M7-A8. CLSI, Wayne, PA 19087. January 2009.

16 HOW SUPPLIED/STORAGE AND HANDLING

Each kit for a 28-day course of CAYSTON contains 84 sterile vials of CAYSTON and 88 ampules of sterile diluent packed in 2 cartons, each carton containing a 14-day supply. The four additional diluent ampules are provided in case of spillage.

Package Configuration | Dosage Strength | NDC
28-Day Kit | 75 mg | 61958-0901-1

STORAGE AND HANDLING

CAYSTON vials and diluent ampules should be stored in the refrigerator at 2 °C to 8 °C (36 °F to 46 °F) until needed. Once removed from the refrigerator, CAYSTON and diluent may be stored at room temperature (up to 25 °C/77 °F) for up to 28 days. Do not separate the CAYSTON vials from the diluent ampules. CAYSTON should be protected from light.

Do not use CAYSTON if it has been stored at room temperature for more than 28 days. Do not use CAYSTON beyond the expiration date stamped on the vial. Do not use diluent beyond the expiration date embossed on the ampule.

CAYSTON should be used immediately upon reconstitution. Do not reconstitute more than one dose at a time.

Do not use diluent or reconstituted CAYSTON if it is cloudy or if there are particles in the solution.

17 PATIENT COUNSELING INFORMATION

Advise the patient to read the FDA-approved patient labeling (Patient Information and Instructions for Use).

Allergic Reactions

Advise patients to tell their healthcare provider immediately if they believe they are experiencing new or worsening symptoms or believe they are having an allergic reaction to CAYSTON [see Warnings and Precautions (5.1)].

Development of Drug-Resistant Bacteria

Counsel patients that antibacterial drugs including CAYSTON should only be used to treat bacterial infections. They do not treat viral infection (e.g., the common cold). When CAYSTON is prescribed to treat a bacterial infection, inform patients that although it is common to feel better early in the course of therapy, the medication should be taken exactly as directed. Skipping doses or not completing the full course of therapy may (1) decrease the effectiveness of the immediate treatment and (2) increase the likelihood that bacteria will develop resistance and will not be treatable by CAYSTON or other antibacterial drugs in the future [see Warnings and Precautions (5.4)].

Reconstitution and Administration

Advise patients that:

- CAYSTON is for inhalation use only and should only be administered using the Altera Nebulizer System.
- CAYSTON should only be reconstituted with the provided diluent. Instruct patients not to mix other drugs with CAYSTON in the Altera Nebulizer System.

Advise patients to:

- use a bronchodilator prior to administration of CAYSTON.
- complete the full 28-day course of CAYSTON even if they are feeling better.

Advise patients taking several inhaled medications to use the medications in the following order: bronchodilator, mucolytics, and lastly, CAYSTON.

Missed Dose

Inform the patient that if they miss a dose, they should take all 3 daily doses as long as the doses are at least 4 hours apart.

CAYSTON is a trademark of Gilead Sciences, Inc. All other trademarks referenced herein are the property of their respective owners.

© 2019 Gilead Sciences, Inc. All rights reserved.

50-814-GS-004

PATIENT INFORMATION
CAYSTON® (kay-stun)
(aztreonam for inhalation solution)
for oral inhalation use

What is CAYSTON?
CAYSTON is a prescription medicine that is used to improve breathing symptoms in people with cystic fibrosis (CF) who have a lung infection caused by a bacterium called Pseudomonas aeruginosa. CAYSTON contains an antibacterial medicine called aztreonam.

- CAYSTON is only for infections caused by bacteria. It is not for infections caused by viruses, such as the common cold.

It is not known if CAYSTON is safe and effective:

- in children under 7 years of age
- in people who have an FEV1 less than 25% or greater than 75% predicted
- in people who are colonized with a bacterium called Burkholderia cepacia

Do not take CAYSTON if you are allergic to aztreonam, or any of the ingredients in CAYSTON.
See the end of this Patient Information for a complete list of ingredients in CAYSTON.

Before you take CAYSTON, tell your healthcare provider about all of your medical conditions, including if you:

- are allergic to any antibiotics.
- are pregnant or plan to become pregnant. It is not known if CAYSTON can harm your unborn baby.
- are breastfeeding or plan to breastfeed. CAYSTON can pass into your breastmilk. Talk with your healthcare provider about the best way to feed your baby while you are taking CAYSTON.

Tell your healthcare provider about all the medicines you take, including prescription and over-the-counter medicines, vitamins, and herbal supplements.
Some medicines may affect how CAYSTON works.

How should I take CAYSTON?

- See the step-by-step Instructions for Use about the right way to take your CAYSTON.
- Take CAYSTON exactly as your healthcare provider tells you. Do not change your dose or stop taking CAYSTON unless your healthcare provider tells you to.
- The dose for both adults and children 7 years of age and older is:
  - 1 single-use vial of CAYSTON, mixed with 1 ampule of saline (diluent) inhaled 3 times a day using a hand-held Altera Nebulizer System.
- Each dose of CAYSTON should be taken at least 4 hours apart (for example: morning, after school, and before bed).
- CAYSTON should be taken for 28 days.
- CAYSTON is taken as a breathing treatment (inhalation) with the Altera Nebulizer System. Do not use any other nebulizer for your CAYSTON treatment.
- Do not mix or dilute CAYSTON with any other medicines in your Altera Nebulizer System.
- Do not mix CAYSTON with the saline until right before you are ready to use it.
- Do not mix more than 1 dose of CAYSTON at a time.
- Each treatment should take about 2 to 3 minutes.
- If you miss a dose of CAYSTON, you can still take all 3 daily doses as long as they are at least 4 hours apart.
- You should use an inhaled bronchodilator (a type of medicine used to relax and open your airways) before taking a dose of CAYSTON. If you do not have an inhaled bronchodilator, ask your healthcare provider to prescribe one for you.
  - Take short-acting bronchodilators between 15 minutes and 4 hours before you take your dose of CAYSTON
  - Take long-acting bronchodilators between 30 minutes and 12 hours before you take your dose of CAYSTON
- If you are taking several medicines or treatments to treat your cystic fibrosis, you should take your medicines or other treatments in this order:
  1) bronchodilator
  2) mucolytics (medicines to help clear mucus from your lungs)
  3) CAYSTON
- After taking CAYSTON for 28 days, you should stop taking it and wait 28 days. Complete the full 28-day course of CAYSTON even if you are feeling better. It is important that you keep to the 28-day on, 28 day off cycle.
- If you skip doses or do not finish the full 28-day course of CAYSTON, your infection may not be fully treated and CAYSTON may not work as well as a treatment for infections in the future.

What are the possible side effects of CAYSTON?
CAYSTON may cause serious side effects, including:

- Severe allergic reactions. Stop your treatment with CAYSTON and call your healthcare provider right away if you have any symptoms of an allergic reaction, including:
  - Rash or swelling of your face
  - Throat tightness
- Trouble breathing right after treatment with CAYSTON (bronchospasm). Tell your healthcare provider right away if you get any of these symptoms of bronchospasm with using CAYSTON:
  - shortness of breath with wheezing
  - coughing and chest tightness
  To decrease the chance of this happening, be sure to use your inhaled bronchodilator medicine before each treatment with CAYSTON. See "How should I take CAYSTON?"

The most common side effects of CAYSTON include:

- cough
- nasal congestion
- wheezing
- sore throat

- fever. Fever may be more common in children than in adults.
- chest discomfort
- stomach area (abdominal) pain
- vomiting

Other possible side effects of CAYSTON include swelling or pain in joints.
Tell your healthcare provider if you have any new or worsening symptoms while taking CAYSTON. Tell your healthcare provider about any side effect that bothers you or that does not go away.

These are not all the possible side effects of CAYSTON.
Call your healthcare provider for medical advice about side effects. You may report side effects to FDA at 1-800-FDA-1088.

How should I store CAYSTON?

- Each CAYSTON kit contains enough single-use vials of CAYSTON and ampules of saline for 28 days of treatment. There are 4 extra saline ampules in case some saline spills.
- Always keep your CAYSTON and saline together.
- Store CAYSTON and saline in the refrigerator between 36 °F to 46 °F (2 °C to 8 °C) until needed.
- When you remove CAYSTON and saline from the refrigerator, they may be stored at room temperature (up to 77 °F) for up to 28 days. Do not use any CAYSTON that has been stored at room temperature for more than 28 days.
- Keep CAYSTON away from light.
- Do not use CAYSTON after the expiration date on the vial. Do not use the saline after the expiration date on the ampule.

Keep CAYSTON and all medicines out of the reach of children.

General information about the safe and effective use of CAYSTON
Medicines are sometimes prescribed for purposes other than those listed in a Patient Information leaflet. Do not use CAYSTON for a condition for which it was not prescribed. Do not give CAYSTON to other people, even if they have the same symptoms that you have. It may harm them. You can ask your pharmacist or healthcare provider for information about CAYSTON that is written for health professionals.

What are the ingredients in CAYSTON?
Active ingredient: aztreonam
Inactive ingredient: lysine, sodium chloride (diluent)
Manufactured and distributed by: Gilead Sciences, Inc. Foster City, CA 94404
CAYSTON is a registered trademark of Gilead Sciences, Inc. ©2019 Gilead Sciences, Inc. All rights reserved.
50-814-GS-004
For more information, call 1-877-7CAYSTON (1-877-722-9786).

This Patient Information has been approved by the U.S. Food and Drug Administration

Rev November 2019

PATIENT INSTRUCTIONS FOR USE

CAYSTON®
(aztreonam for inhalation solution)
for oral inhalation use

Be sure that you read, understand and follow the Patient Instructions for Use below for the right way to take CAYSTON. If you have any questions, ask your healthcare provider or pharmacist.

You will need the following supplies (Figure 1):

- 1 amber colored CAYSTON vial covered by a metal seal with a blue cap
- 1 ampule of saline (diluent)
- Altera Nebulizer System

Figure 1

Check to make sure that your Altera Nebulizer System works properly before starting your treatment with CAYSTON. See the manufacturer's instructions for use that comes with your Altera Nebulizer System. This should have complete information about how to put together (assemble), prepare, use, and care for your Altera Nebulizer System.

Preparing your CAYSTON for Inhalation

Step 1. Mix (reconstitute) CAYSTON with the saline only when ready to take a dose. Take 1 amber vial of CAYSTON and 1 ampule of saline from the carton. Separate the saline ampules by gently pulling apart.
Step 2. Look at the ampule of saline. If it looks cloudy do not use it. Throw away this ampule and get another ampule of saline.
Step 3. Gently tap the vial so that the powder settles to the bottom of the vial. This helps you get the proper dose of medicine. Follow Step A to Step D in Figure 2 below to open the vial:

Step A: With the blue cap tab facing toward you, place the vial on a flat surface. Using one hand to hold the vial steady, use the other hand to slowly flip up the blue cap. | Step B: Pull the blue cap down to a flat (horizontal) position (where the bottom of the blue cap faces up), to prepare the metal seal for removal. Do not completely tear through the metal seal.
Step C: While continuing to hold the vial steady with one hand, use the other hand to slowly pull the blue cap in a counterclockwise direction. Do not twist the blue cap. | Step D: When the metal seal opens, continue to slowly pull the blue cap in a counterclockwise direction until the metal seal is completely removed.
Figure 2

Step 4. Safely throw away (dispose of) the metal seal in household garbage. Carefully remove (but do not yet discard) the rubber stopper.
Step 5. Open the ampule of saline by twisting off the tip. Squeeze out the contents completely into the vial (Figure 3). Next, close the vial with the rubber stopper and gently swirl the vial until the powder has completely dissolved and the liquid is clear.
  Figure 3
Step 6. After mixing CAYSTON with the saline, check to make sure the diluted medicine is clear. If it is cloudy or has particles in it, do not use this medicine. Throw away this dose of medicine and start over again with a new vial of CAYSTON and a new ampule of saline.
Step 7. Use CAYSTON right away after you mix with the saline.

Taking your CAYSTON Treatment

See the manufacturer's instructions for use that comes with your Altera Nebulizer System for complete instructions on taking a treatment, and how to clean and disinfect your Altera Nebulizer Handset.

Step 8. Make sure the handset is on a flat, stable surface.
Step 9. Remove the rubber stopper from the vial, then pour all of the mixed CAYSTON and saline into the Medication Reservoir of the handset (Figure 4). Be sure to completely empty the vial, gently tapping the vial against the side of the Medication Reservoir if necessary. Close the Medication Reservoir (Figure 5).
  Figure 4
  Figure 5
Step 10. Begin your treatment by sitting in a relaxed, upright position. Hold the handset level, and place the Mouthpiece in your mouth. Close your lips around the Mouthpiece (Figure 6).
  Figure 6
Step 11. Breathe in and out normally (inhale and exhale) through the Mouthpiece. Avoid breathing through your nose. Continue to inhale and exhale comfortably until the treatment is finished.
Step 12. The empty vial, stopper and saline ampule should be disposed of in household garbage upon completion of dosing.

This Instructions for Use has been approved by the U.S. Food and Drug Administration.

Manufactured by: Gilead Sciences, Inc., Foster City, CA 94404

CAYSTON is a trademark of Gilead Sciences, Inc. All other trademarks referenced herein are the property of their respective owners.

© 2019 Gilead Sciences, Inc. All rights reserved.

50-814-GS-004

Revised: November 2019

PACKAGE LABEL

Principal Display Panel - Cayston 28 Day Carton - Representative Label

NDC 61958-0901-1

GILEAD

Cayston®
(aztreonam for
inhalation solution)

75 mg/vial

For Oral Inhalation Only

Store Refrigerated, 2 °C to 8 °C (36 °F to 46 °F)

Contains:
84 Single-Use Vials of Aztreonam for Inhalation Solution
88 Diluent Ampules of Sodium Chloride 0.17%, 1 mL
(4 extra ampules provided in case of spillage)

For use only with the Altera® Nebulizer System

28-Day Supply

Rx only